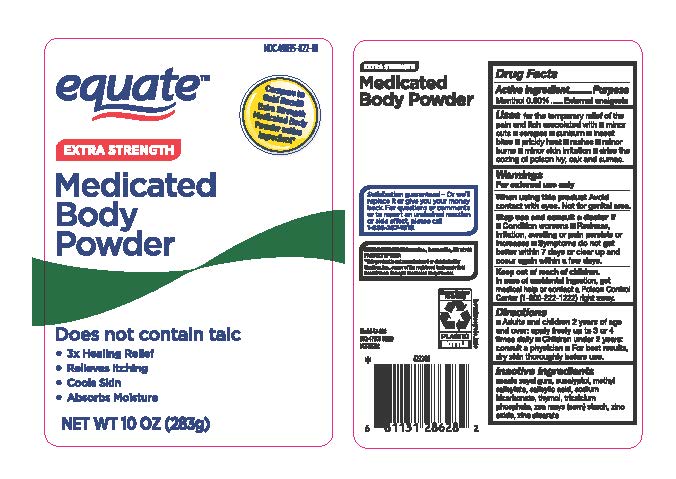 DRUG LABEL: Medicated Body Extra Strength
NDC: 49035-822 | Form: POWDER
Manufacturer: Walmart Stores Inc
Category: otc | Type: HUMAN OTC DRUG LABEL
Date: 20251227

ACTIVE INGREDIENTS: MENTHOL 2.26 g/283 g
INACTIVE INGREDIENTS: SODIUM BICARBONATE; TRICALCIUM PHOSPHATE; ACACIA; EUCALYPTUS OIL; MENTHYL SALICYLATE, (+/-)-; SALICYLIC ACID; THYMOL; ZINC STEARATE; ZINC OXIDE; ZEA MAYS WHOLE; ACACIA SEYAL WHOLE

Medicated Body Powder Extra Strength

Drug Facts Active Ingredients

Menthol 0.80 %

Purpose

External Analgesic

Uses

for the temporary relief of the pain and itch associated with

- minor cuts
- scrapes
- sunburn
- insect bites
- prickly heat
- rashes
- minor burns
- minor skin irritations
- dries the oozing of poison ivy, oak and sumac.

Warnings

For external use only

When usin this product

Avoid contact with eyes. Not for genital area.

Stop use and ask a doctor if

- condition worsens
- Redness, irritation, swelling or pain persists or increases
- symptoms do not get better within 7 days or clear up and occur again within a few days

Keep out of reach of children. In case of accidental ingestion, get medical help or contact a Poison Control Center (1-800-222-1222) right away.

Directions

- adults and children 2 years and older, apply freely up to 3 or 4 times daily
- Children under 2 years: consult a physician
- for best results, dry skin thoroughly before use

Inactive Ingredients

Acacia, seyal gum, eucalyptol, methyl salicylate, salicylic acid, sodium bicarbonate, Thymol, tricalcium phosphate, Zea mays (corn) starch, zinc oxide, zinc stearate.

Medicated Body Powder Extra Strength

NDC 49035-295-10

equate™

Compare to GoldBond® Medicated Body Powder Active Ingredients

Medicated Body Powder

4 X Relief

- Relieves Itcing
- Cools Skin
- Absorbs Moisture
- Helps Protect skin

Menthol 0.15%

NET WT 10 OZ (283g)

Medicated Body Powder

Satisfaction guarenteed- or we'll replace it or give you your money back.

For questions or comments or to report an undesired reaction or side effect, please call 1-888-287-1915

DISTRIBUTED BY:
Wal-Mart Stores, Inc.,

Bentonville, AR 72716

PRODUCT OF IINDIA

*This product is not manufactured or distributed by Chattem, Inc., owner of the registered trademark Gold Bond® Medicated body Powder.